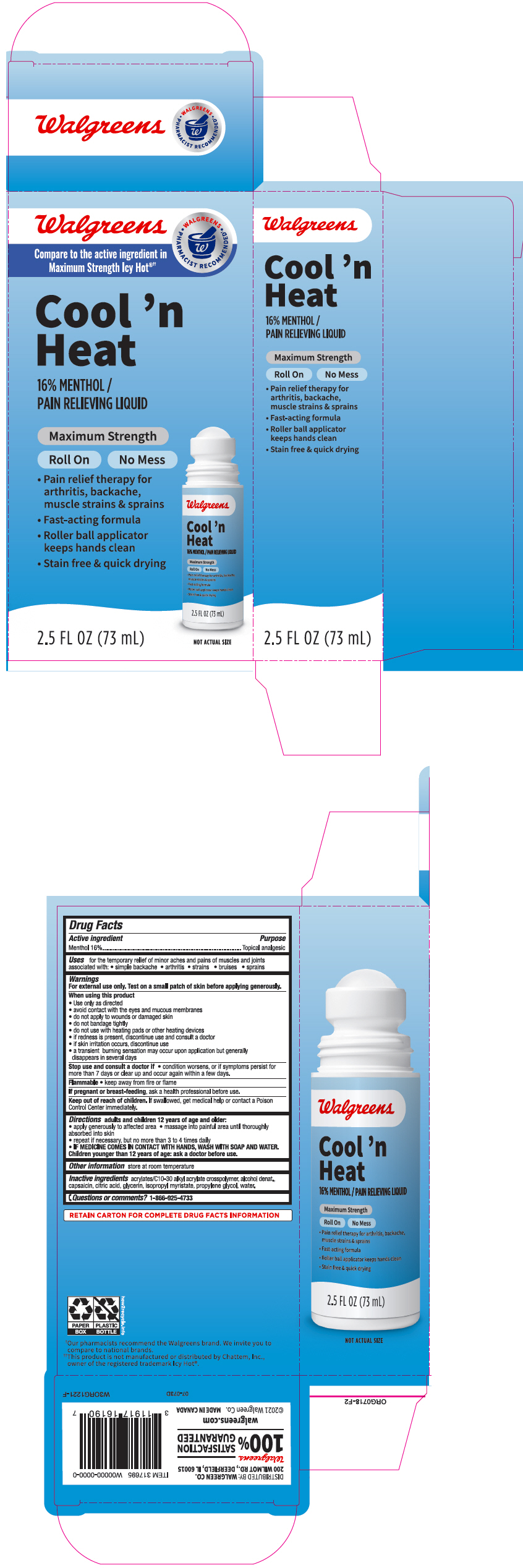 DRUG LABEL: Walgreen Cool n Heat Maximum Strength Pain Relieving
NDC: 0363-4837 | Form: LIQUID
Manufacturer: Walgreen Company
Category: otc | Type: HUMAN OTC DRUG LABEL
Date: 20241104

ACTIVE INGREDIENTS: MENTHOL, UNSPECIFIED FORM 160 mg/1 mL
INACTIVE INGREDIENTS: ALCOHOL; CAPSAICIN; CITRIC ACID MONOHYDRATE; GLYCERIN; ISOPROPYL MYRISTATE; PROPYLENE GLYCOL; WATER

Walgreen Cool 'n Heat Maximum Strength Pain Relieving Liquid
Topical Analgesic

Drug Facts

Active ingredients

Menthol 16%

Purpose

Topical analgesic

Uses

for the temporary relief of minor aches and pains of muscles and joints associated with:

- simple backache
- arthritis
- strains
- bruises
- sprains

Warnings

For external use only. Test on a small patch of skin before applying generously.

When using this product

- use only as directed
- avoid contact with the eyes and mucous membranes
- do not apply to wounds or damaged skin
- do not bandage tightly
- do not use with heating pads or other heating devices
- if redness is present, discontinue use and consult a doctor
- if skin irritation occurs, discontinue use
- a transient burning sensation may occur upon application but generally disappears in several days

Stop use and consult a doctor if

- condition worsens, or if symptoms persist for more than 7 days or clear up and occur again within a few days.

Flammable

- keep away from fire or flame

PREGNANCY OR BREAST FEEDING

If pregnant or breast-feeding, ask a health professional before use.

Keep out of reach of children. If swallowed, get medical help or contact a Poison Control Center immediately.

Directions

adults and children 12 years of age and older:

- apply generously to affected area
- massage into painful area until thoroughly absorbed into skin
- repeat if necessary, but not more than 3 to 4 times daily
- IF MEDICINE COMES IN CONTACT WITH HANDS, WASH WITH SOAP AND WATER.

Children 12 years or younger: ask a doctor before use.

Other information

store at room temperature

Inactive ingredients

acrylates/C10-30 alkyl acrylate crosspolymer, alcohol denat., capsaicin, citric acid, glycerin, isopropyl myristate, propylene glycol, water.

Questions or comments?

1-866-925-4733

DISTRIBUTED BY: WALGREEN CO.
200 WILMOT RD., DEERFIELD, IL 60015

PRINCIPAL DISPLAY PANEL - 73 mL Bottle Carton

Walgreens

• WALGREENS •
PHARMACIST RECOMMENDED†

Compare to the active ingredient in
Maximum Strength Icy Hot®††

Cool 'n
Heat

16% MENTHOL /
PAIN RELIEVING LIQUID

Maximum Strength

Roll On
No Mess

- Pain relief therapy for
  arthritis, backache,
  muscle strains & sprains
- Fast-acting formula
- Roller ball applicator
  keeps hands clean
- Stain free & quick drying

NOT ACTUAL SIZE

2.5 FL OZ (73 mL)